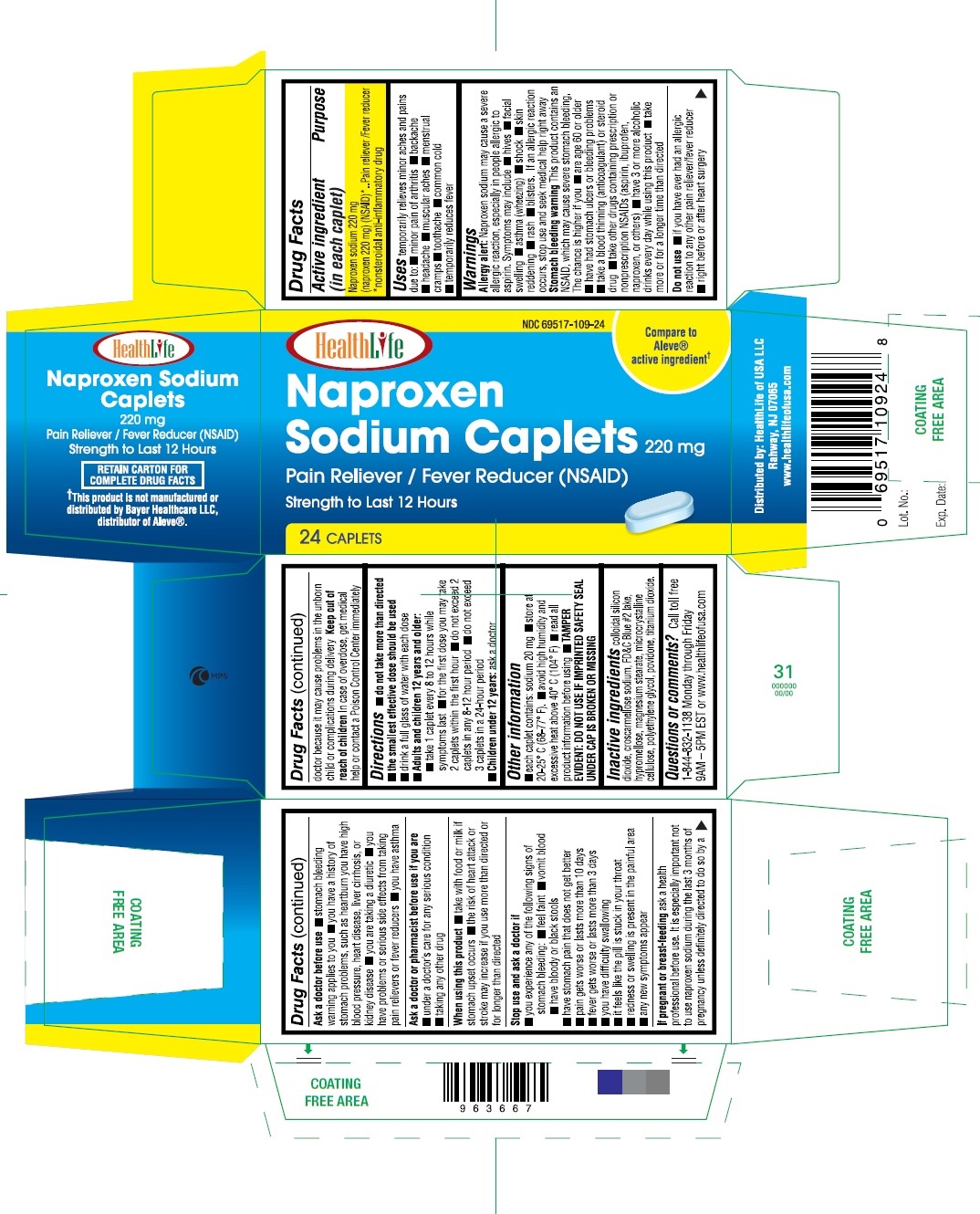 DRUG LABEL: All Day Pain Relief
NDC: 69517-109 | Form: TABLET
Manufacturer: HealthLife of USA LLC
Category: otc | Type: HUMAN OTC DRUG LABEL
Date: 20170601

ACTIVE INGREDIENTS: NAPROXEN SODIUM 220 mg/1 1
INACTIVE INGREDIENTS: HYPROMELLOSES; FD&C BLUE NO. 2; POVIDONE K30; STARCH, CORN; SODIUM STARCH GLYCOLATE TYPE A POTATO; CELLULOSE, MICROCRYSTALLINE; POLYETHYLENE GLYCOL 400; STEARIC ACID; TITANIUM DIOXIDE

All Day Pain Relief - Naproxen Sodium Tablets, 220 mg

Drug Facts

ACTIVE INGREDIENT

Active ingredient (in each caplet) Purpose

Naproxen Sodium 220 mg

(naproxen 200mg) (NSAID)* ....................Pain reliever / Fever reducer

*nonsteroidal anti-inflammatory drug

Uses

■ temporarily relieves minor aches and pains due to:

■ minor pain of arthritis ■ muscular aches ■ backache ■ headache

■ menstrual cramps ■ toothache ■ the common cold

■ temporarily reduces fever

Warnings

Allergy alert:

Naproxen sodium may cause a severe allergic reaction, especially in people allergic to aspirin. Symptoms may include:

■ hives ■ facial swelling ■ asthma (wheezing) ■ shock

■ skin reddening ■ rash ■ blisters

If an allergic reaction occurs, stop use and seek medical help right away.

Stomach bleeding warning:

This product contains an NSAID, which may cause severe stomach bleeding. The chance is higher if you:

■ are age 60 or older

■ have had stomach ulcers or bleeding problems

■ take a blood thinning (anticoagulant) or steroid drug

■ take other drugs containing prescription or nonprescription NSAIDs (aspirin, ibuprofen, naproxen, or others)

■ have 3 or more alcoholic drinks every day while using this product

■ take more or for a longer time than directed

Do not use

■ if you have ever had an allergic reaction to any other pain reliever/fever reducer

■ right before or after heart surgery

Ask a doctor before use if

■ the stomach bleeding warning applies to you

■ you have a history of stomach problems, such as heartburn

■ you have high blood pressure, heart disease, liver cirrhosis, or kidney disease

■ you are taking a diuretic

■ you have problems or serious side effects from taking pain relievers or fever reducers

■ you have asthma

Ask a doctor or pharmacist before use if you are

■ under a doctor's care for any serious condition

■ taking any other drug

When using this product

■ take with food or milk if stomach upset occurs

■ the risk of heart attack or stroke may increase if you use more than directed or for longer than directed

Stop use and ask a doctor if

■ you experience any of the following signs of stomach bleeding:

■ feel faint ■ vomit blood ■ have bloody or black stools

■ have stomach pain that does not get better

■ pain gets worse or lasts more than 10 days

■ fever gets worse or lasts more than 3 days

■ you have difficulty swallowing

■ it feels like the pill is stuck in your throat

■ redness or swelling is present in the painful area

■ any new symptoms appear

PREGNANCY OR BREAST FEEDING

If pregnant or breast-feeding, ask a health professional before use. It is especially important not to use naproxen sodium during the last 3 months of pregnancy unless definitely directed to do so by a doctor because it may cause problems in the unborn child or complications during delivery.

Keep out of reach of children.

In case of overdose, get medical help or contact a Poison Control Center (1-800-222-1222) right away. Quick medical attention is critical for adults as well as for children even if you do not notice any signs or symptoms.

Directions

■ do not take more than directed

■ the smallest effective dose should be used

■ drink a full glass of water with each dose

Adults and children 12 years and older:

■ take 1 tablet every 8 to 12 hours while symptoms last

■ for the first dose you may take 2 tablets within the first hour

■ do not exceed 2 tablets in any 8 to 12-hour period

■ do not exceed 3 tablets in a 24-hour period

Children under 12 years

■ ask a doctor

Other information

■ each tablet contains: sodium 20 mg

■ store at 20-25° C (68-77° F).

■ avoid high humidity and excessive heat above 40° C (104° F)

■ read all product information before using

■ TAMPER EVIDENT: DO NOT USE IF IMPRINTED SAFETY SEAL UNDER CAP IS BROKEN OR MISSING

Inactive ingredients

colloidal silicon dioxide, croscarmellose sodium, FD&C Blue #2 lake, hypromellose, magnesium stearate, microcrystalline cellulose, polyethylene glycol, povidone, titanium dioxide

Questions or comments?

Call toll free 1-844-832-1138 Monday through Friday 9AM – 5PM EST or www.healthlifeofusa.com

PRINCIPAL DISPLAY PANEL

See New Warnings Information & Directions

Compare to the Active Ingredients in Aleve®.

ALL DAY PAIN RELIEF

Naproxen Sodium Tablets, 220 mg